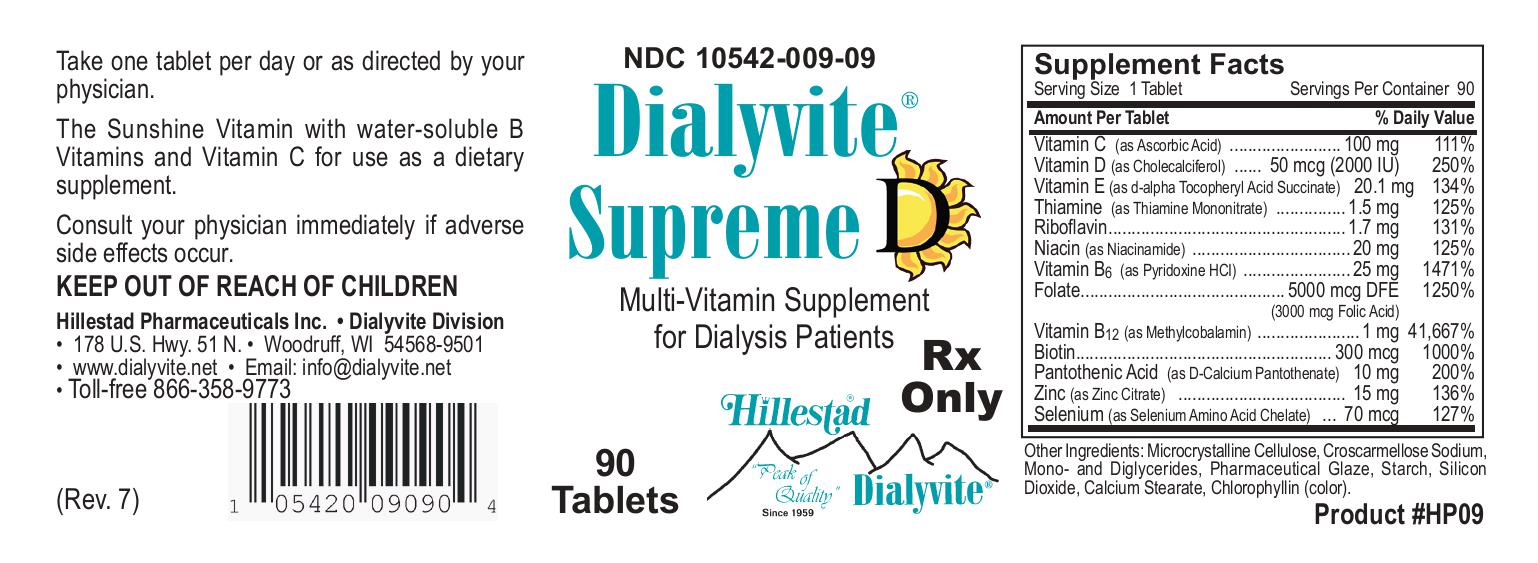 DRUG LABEL: Dialyvite Supreme D
NDC: 10542-009 | Form: TABLET, COATED
Manufacturer: Hillestad Pharmaceuticals USA
Category: prescription | Type: HUMAN PRESCRIPTION DRUG LABEL
Date: 20260127

ACTIVE INGREDIENTS: Ascorbic Acid 100 mg/1 1; Cholecalciferol 2000 [iU]/1 1; .alpha.-tocopherol succinate, d-  30 [iU]/1 1; Thiamine Mononitrate 1.5 mg/1 1; Riboflavin 1.7 mg/1 1; Niacinamide 20 mg/1 1; Pyridoxine Hydrochloride 25 mg/1 1; Folic Acid 3 mg/1 1; Cobalamin 1 mg/1 1; Biotin 300 ug/1 1; Calcium Pantothenate 10 mg/1 1; Zinc Citrate 15 mg/1 1; Selenocysteine 70 ug/1 1
INACTIVE INGREDIENTS: Microcrystalline Cellulose; Croscarmellose Sodium; Glyceryl Monostearate; Shellac; Starch, Corn; Silicon Dioxide; Calcium Stearate; Sodium Copper Chlorophyllin

Dialyvite Supreme D

DESCRIPTION

Dialyvite Supreme D is a prescription folic acid supplement with additional nutrients for kidney dialysis patients. Dialyvite Supreme D is a small, round, light green, coated tablet, with debossed "H" on one side, and bisected on the other side.

Each tablet contains:

Folic Acid.....3 mg

Vitamin C (Ascorbic Acid).....100 mg

Vitamin D (Cholecalciferol).....2000 IU

Vitamin E (D-alpha-Tocopheryl Acid Succinate).....30 IU

Thiamine Mononitrate.....1.5 mg

Riboflavin.....1.7 mg

Niacinamide.....20 mg

Vitamin B6 (Pyridoxine HCl).....25 mg

Vitamin B12 (Methylcobalamin).....1 mg

Biotin.....300 mcg

Pantothenic Acid (Calcium Pantothenate).....10 mg

Zinc (Zinc Citrate).....15 mg

Selenium (Selenium Amino Acid Chelate).....70 mcg

Inactive ingredients:

Microcrystalline Cellulose, Croscarmellose Sodium, Mono- and Diglycerides, Pharmaceutical Glaze, Starch, Silicon Dioxide, Calcium Stearate, Chlorophyllin (color).

INDICATIONS AND USAGE

Dialyvite Supreme D is a prescription folic acid supplement with additional nutrients indicated for use in improving the nutritional status of renal dialysis patients.

CONTRAINDICATIONS

This product is contraindicated in patients with known hypersensitivity to any of the ingredients.

PRECAUTIONS

Folic acid supplementation may obscure pernicious anemia, in that hematologic remission can occur while neurological manifestations progress.

Keep out of reach of children.

ADVERSE REACTIONS

Allergic sensitizations have been reported following oral administration of folic acid.

Consult your physician immediately if adverse side effects occur.

DOSAGE AND ADMINISTRATION

Take one tablet or as directed by your physician, orally.

PRINCIPAL DISPLAY PANEL

NDC 10542-009-09

Dialyvite Supreme D

Multivitamin Supplement for Dialysis Patients

90 Tablets